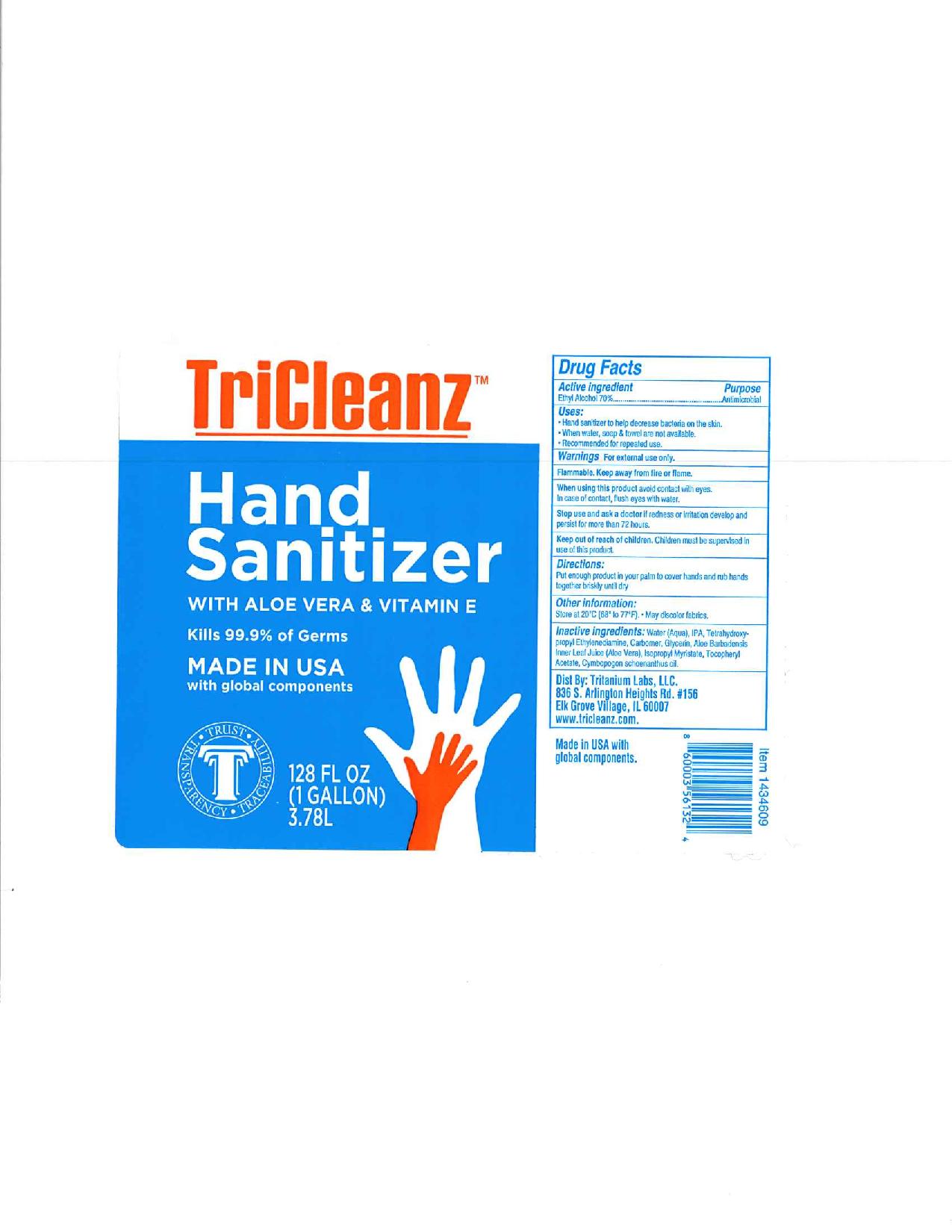 DRUG LABEL: Tritanium Labs Hand Sanitizer
NDC: 77757-121 | Form: GEL
Manufacturer: Tritanium Labs, USA LLC
Category: otc | Type: HUMAN OTC DRUG LABEL
Date: 20200501

ACTIVE INGREDIENTS: ALCOHOL 0.7 g/1 g
INACTIVE INGREDIENTS: EDETOL; WATER; ALOE VERA LEAF; ISOPROPYL ALCOHOL; CYMBOPOGON CITRATUS LEAF; GLYCERIN; CARBOMER 940; ALPHA-TOCOPHEROL ACETATE; ISOPROPYL MYRISTATE

Tritanium Labs Hand Sanitizer

Active Ingredients

Active ingredient | Purpose
Ethyl Alcohol 70% | Antimicrobial

Inactive Ingredients

Water (Aqua)

Aloe Barbadensis Leaf Juice (Stabilized* Aloe Vera Gel)

Isopropyl Alcohol

Glycerin

Tetrahydroxypropyl Ethylenediamine

Acrylates/C10-30 Alkyl Acrylate Crosspolymer

Tocopheryl Acetate
Isopropyl Myristate.

Purpose Section

Uses

• Hand sanitizer to help decrease bacteria on the skin.

• When water, soap & towel are not available.

• Recommended for repeated use.

Warnings

For external use only.

Flammable. Keep away from fire or flame.

Indications & Usage

When using this product, avoid contact with eyes.

In case of contact flush eyes with water.

Stop use and ask a doctor if

- Stop use and ask a doctor if redness or irritation develop and persist for more than 72 hours

Keep out of reach of children. Children must be supervised in use of this product.

Dosage & Administration Directions

Directions

Put enough product in your palm to cover hands and rub hands together briskly until dry.

Other information

- store at 20 °C (68°F to 77°F)
- may discolor certain fabrics